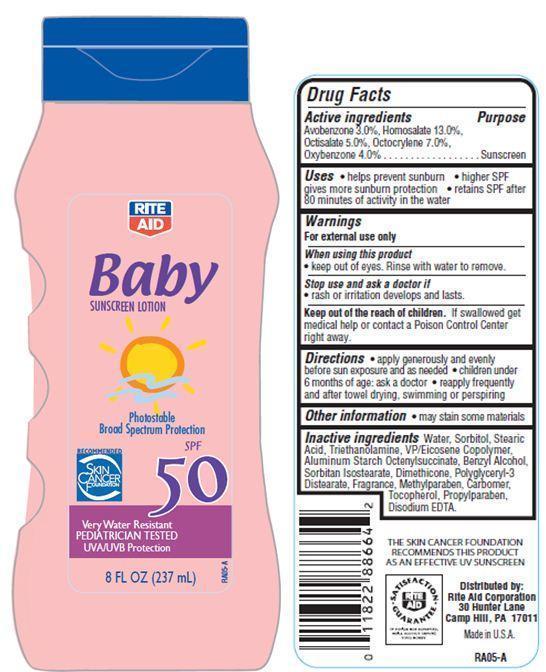 DRUG LABEL: Rite Aid Baby Sunscreen
NDC: 11822-9010 | Form: LOTION
Manufacturer: RITE AID CORPORATION
Category: otc | Type: HUMAN OTC DRUG LABEL
Date: 20121203

ACTIVE INGREDIENTS: AVOBENZONE 3 g/100 g; HOMOSALATE 13 g/100 g; OCTISALATE 5 g/100 g; OCTOCRYLENE 7 g/100 g; OXYBENZONE 4 g/100 g
INACTIVE INGREDIENTS: WATER; SORBITOL; STEARIC ACID; TROLAMINE; ALUMINUM STARCH OCTENYLSUCCINATE; BENZYL ALCOHOL; SORBITAN ISOSTEARATE; DIMETHICONE; METHYLPARABEN; TOCOPHEROL; EDETATE DISODIUM; PROPYLPARABEN

Drug Facts

Active Ingredients

Avobenzone 3.0 %

Homosalate 13.0%

Octisalate 5.0%

Octocrylene 7.0%

Oxybenzone 4.0%

Purpose

Sunscreen

Uses

- helps prevent sunburn
- higher SPF gives more sunburn protection
- retains SPF after 80 minutes of activity in the water

Warnings

For external use only

When using this product

- keep out of eyes. Rinse with water to remove.

Stop use and ask a doctor if

- rash or irritation develops and lasts

Keep out of reach of children

If swallowed, get medical help or contact a Poison Control Center right away.

Directions

- apply generously and evenly before sun exposure and as needed
- children under 6 months of age:ask a doctor
- reapply frequently and after towel drying, swimming or perspiring.

Other Information

- may stain some materials

Inactive Ingredients

Water, Sorbitol, Stearic Acid, Triethanolamine, Aluminum Starch Octenylsuccinate, Benzyl Alcohol, Sorbitan Isostearate, VP/Eicosene Copolymer, Dimethicone, Polyglyceryl-3 Distearate, Carbomer, Tocopherol, Disodium EDTA, Methylparaben, Propylparaben, Fragrance.

Principal Display Panel

RITE AID
Baby
SUNSCREEN LOTION
Photostable
Broad Spectrum Protection
SPF 50
RECOMMENDED
SKIN CANCER
FOUNDATION
Very Water Resistant
PEDIATRICIAN TESTED
UVB/UVA Protection
8 FL OZ (237 mL)